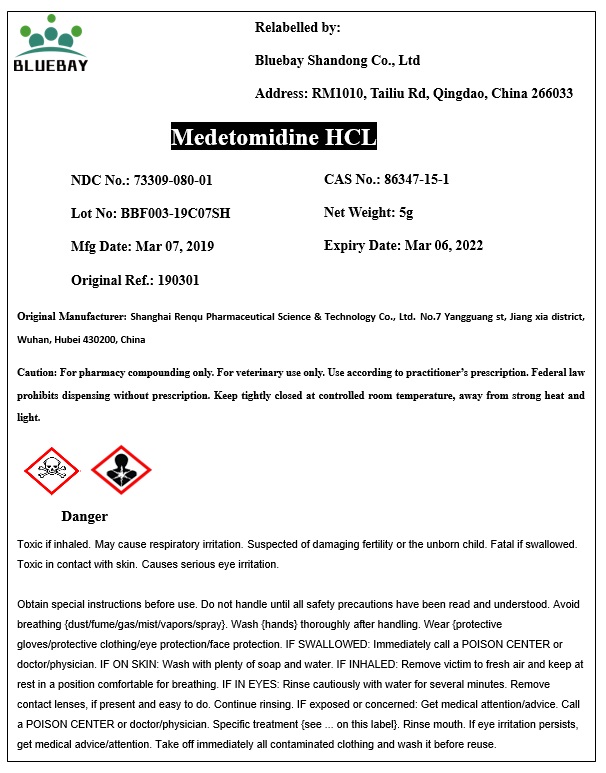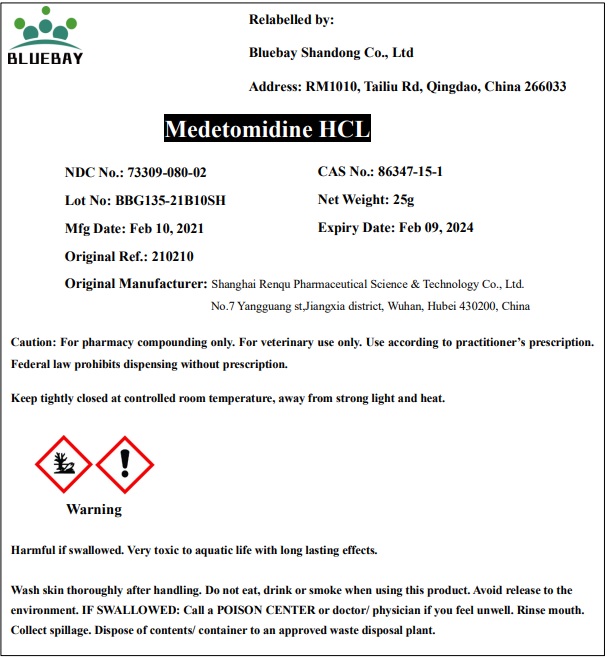 DRUG LABEL: Medetomidine HCL
NDC: 73309-080 | Form: POWDER
Manufacturer: BLUEBAY SHANDONG CO.,LTD
Category: other | Type: BULK INGREDIENT
Date: 20210322

ACTIVE INGREDIENTS: MEDETOMIDINE HYDROCHLORIDE 1 g/1 g

Medetomidine HCL